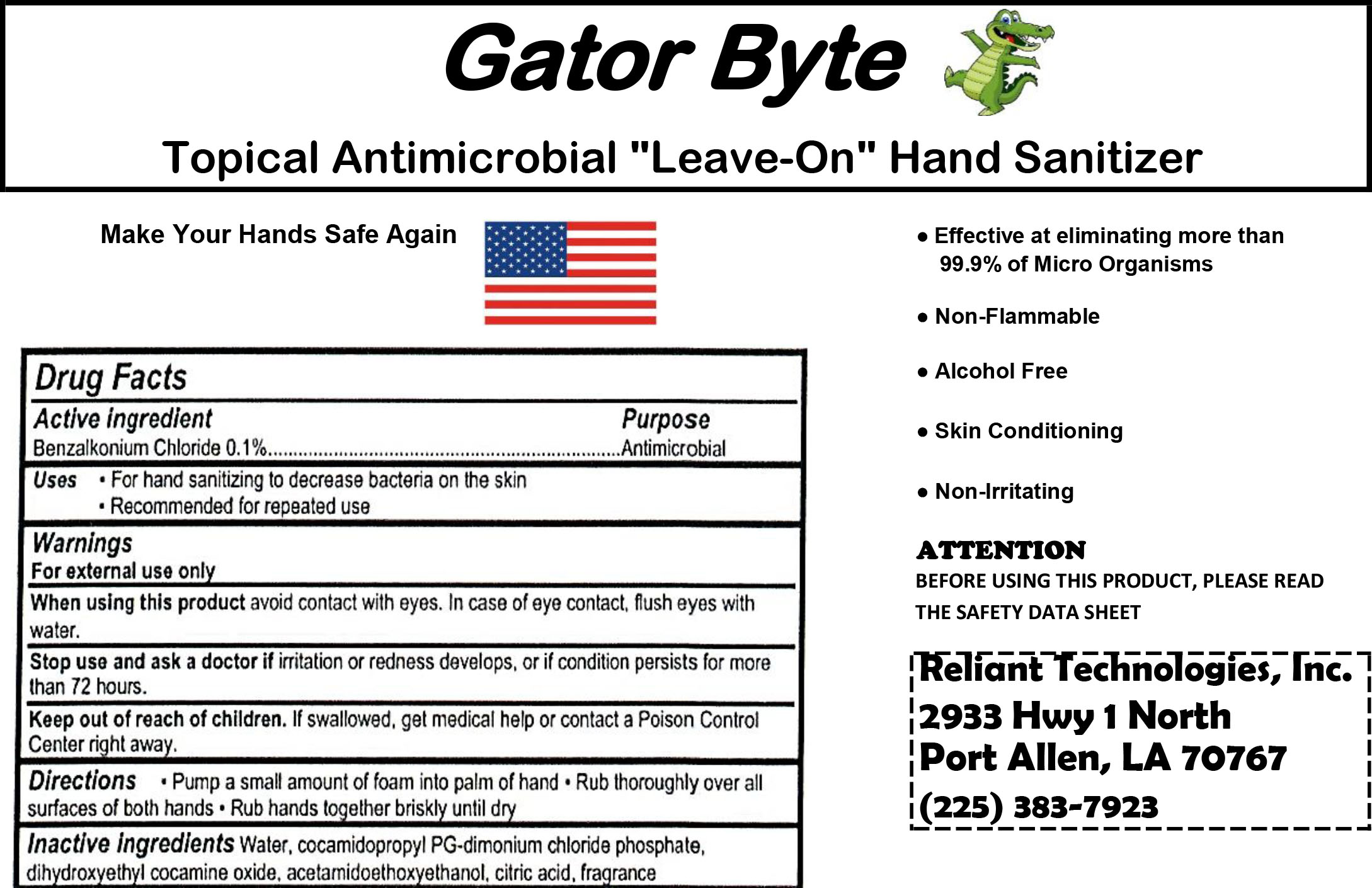 DRUG LABEL: Gator Byte
NDC: 78094-002 | Form: LIQUID
Manufacturer: Reliant Technologies
Category: otc | Type: HUMAN OTC DRUG LABEL
Date: 20200615

ACTIVE INGREDIENTS: BENZALKONIUM CHLORIDE 1.05 g/1000 g
INACTIVE INGREDIENTS: DIHYDROXYETHYL COCAMINE OXIDE 0.45 g/1000 g; LAURTRIMONIUM CHLORIDE 0.5 g/1000 g; WATER 996.82 g/1000 g; GLYCERETH-17 COCOATE 0.5 g/1000 g; ANHYDROUS CITRIC ACID 0.02 g/1000 g; CETRIMONIUM CHLORIDE 0.66 g/1000 g

Non-Alochol Hand Sanitizer